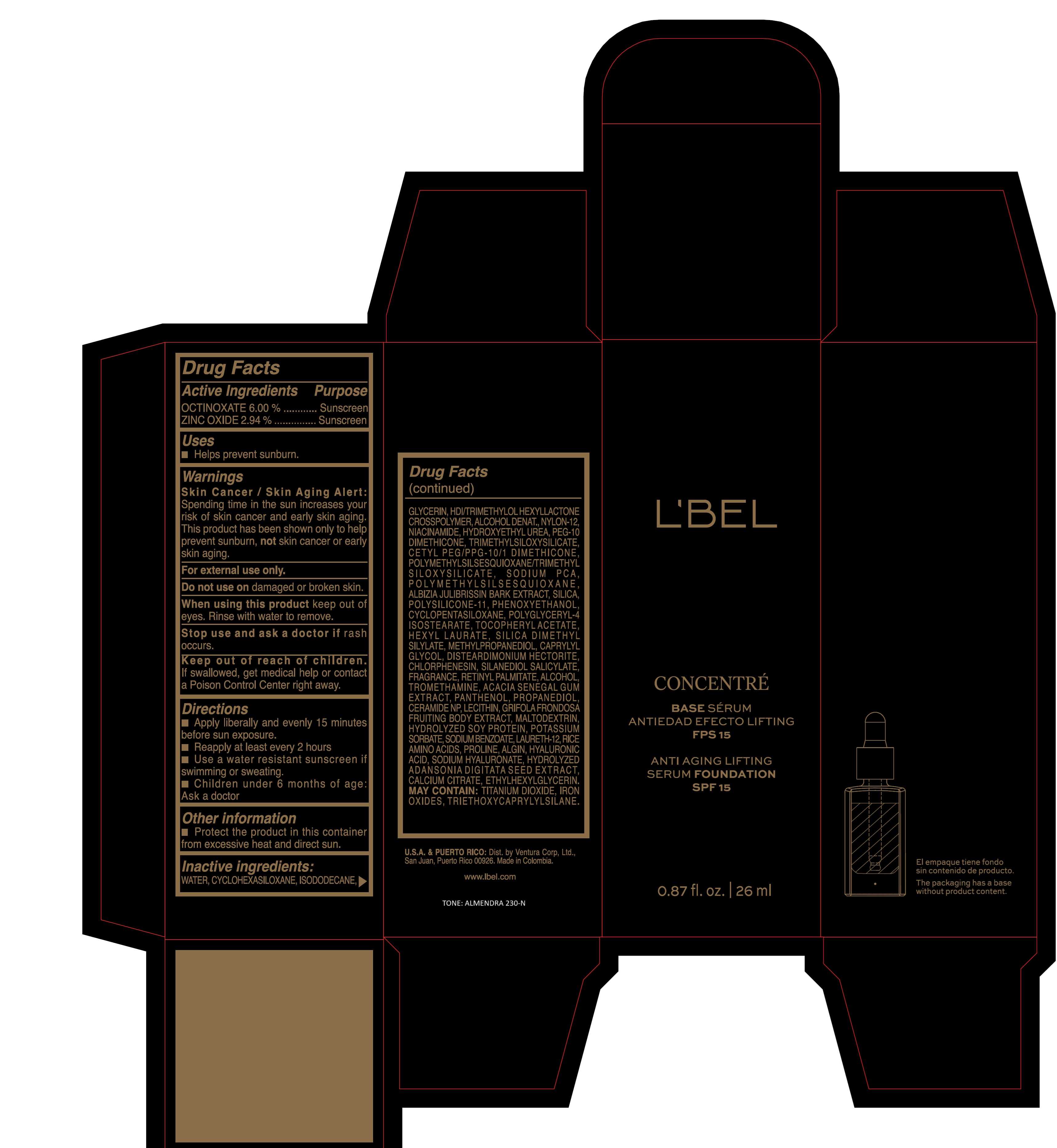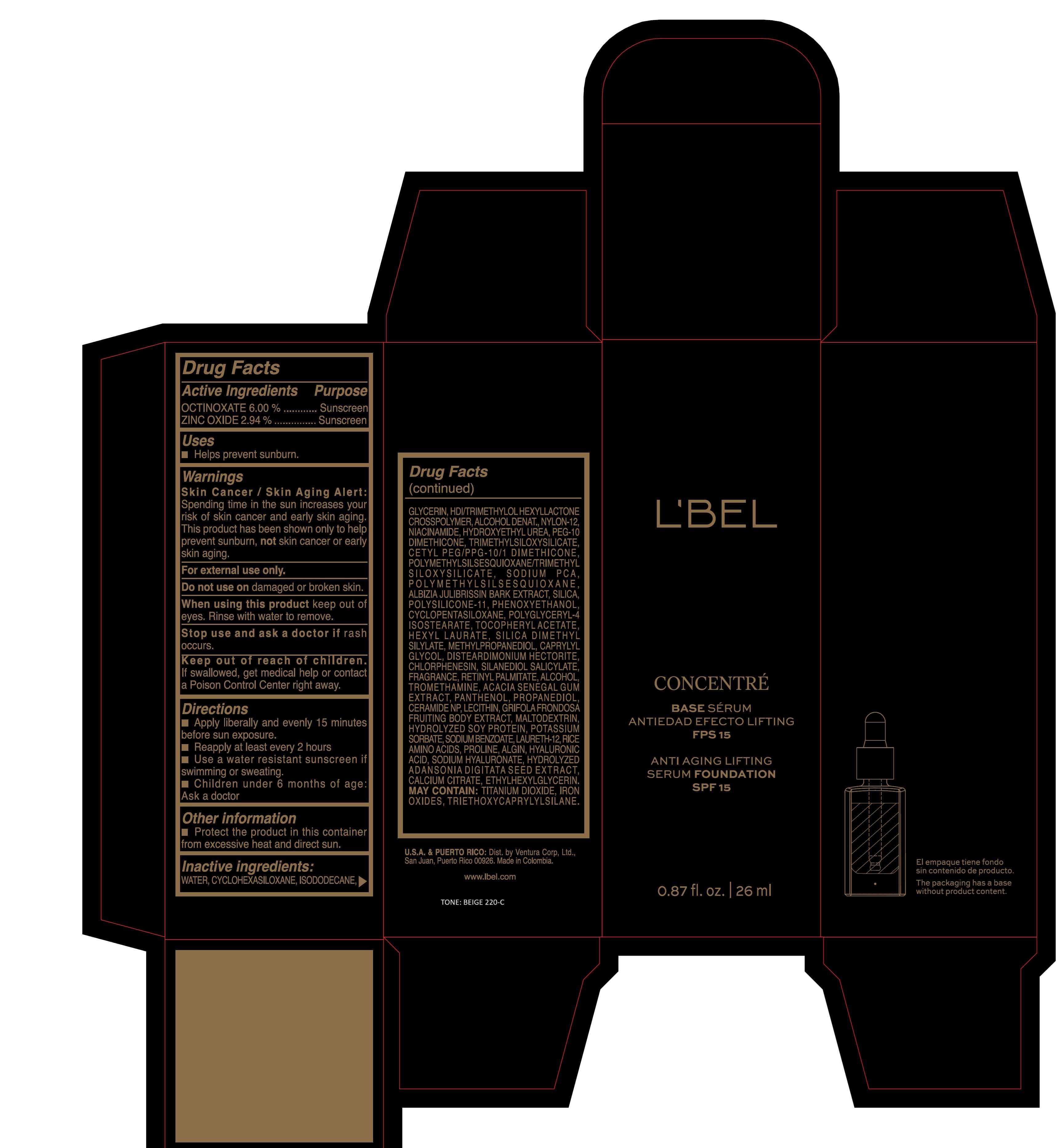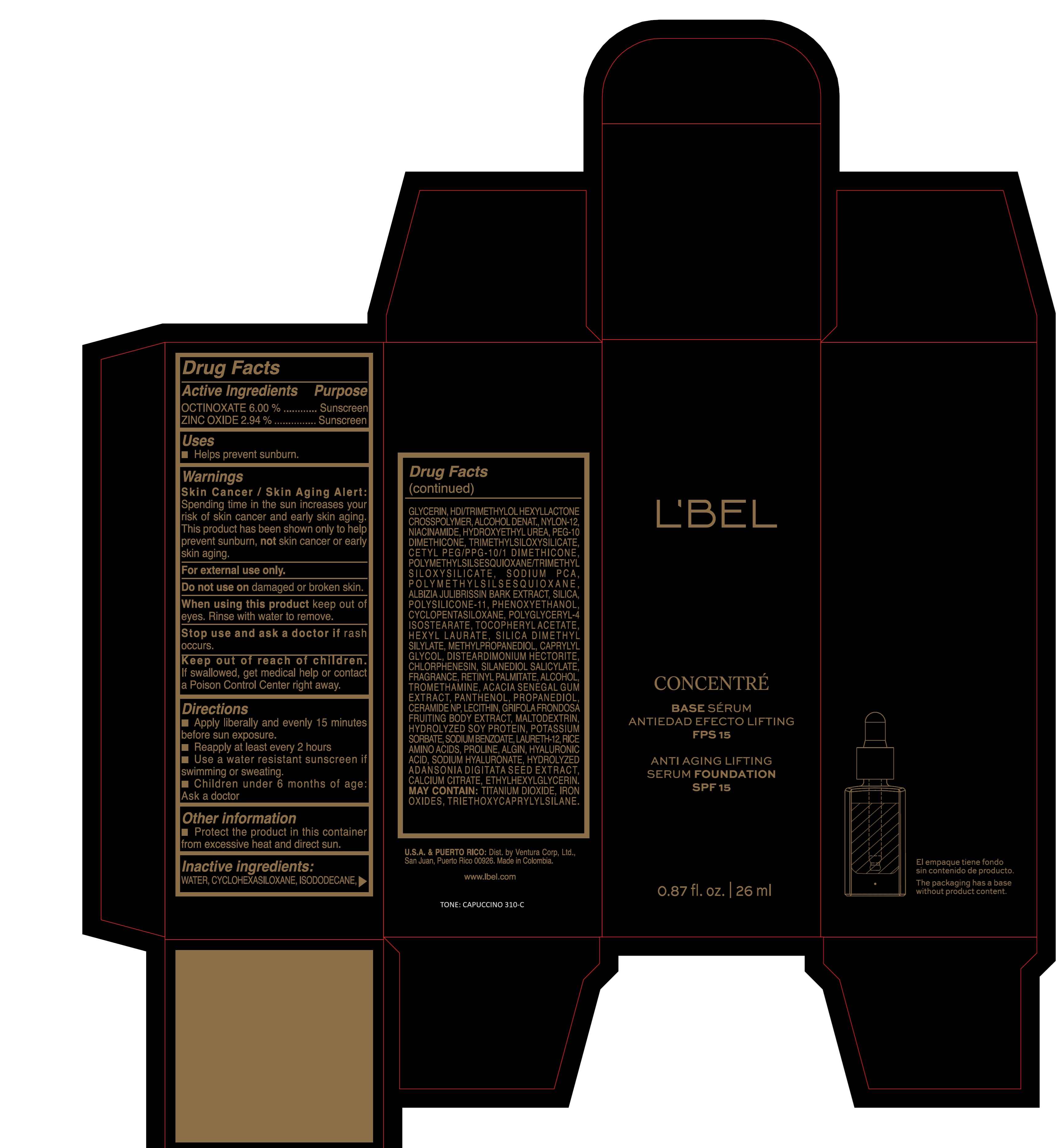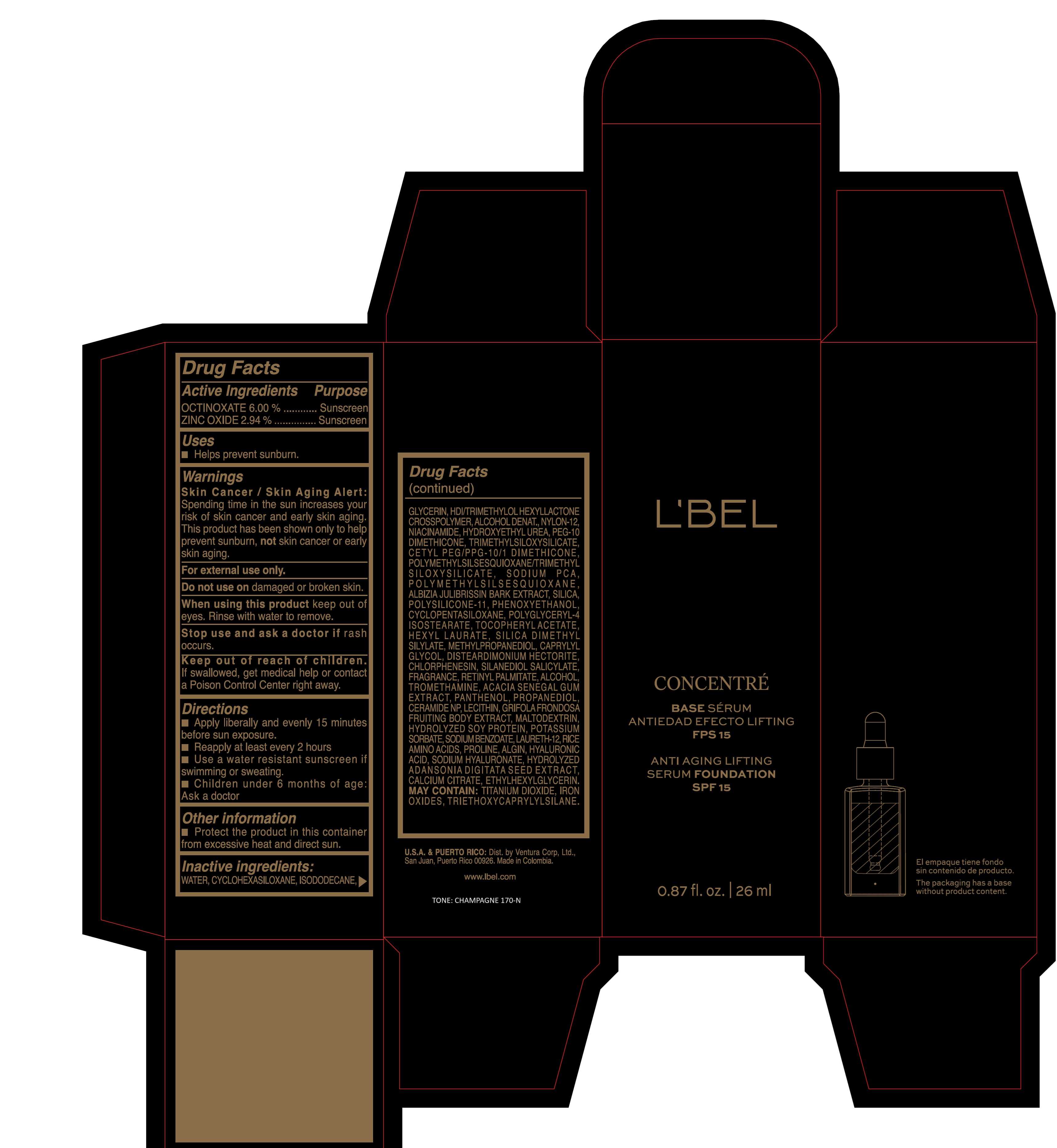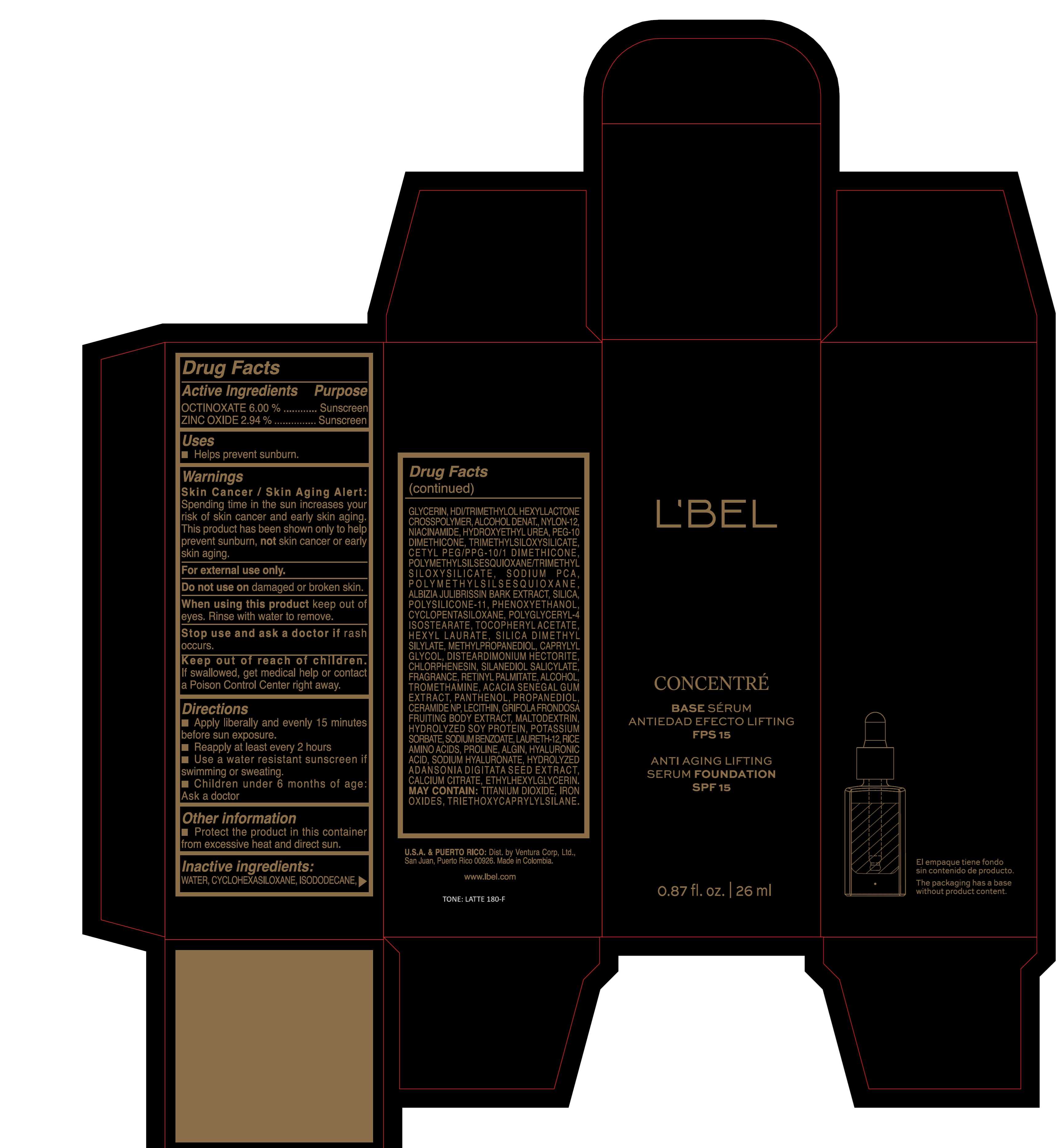 DRUG LABEL: LBEL CONCENTRE BASE SERUM ANTIEDAD EFECTO LIFTING FPS 15 ANTI AGING LIFTING SERUM FOUNDATION SPF 15 CHAMPAGNE 170-N
NDC: 14141-326 | Form: EMULSION
Manufacturer: BEL STAR SA
Category: otc | Type: HUMAN OTC DRUG LABEL
Date: 20250620

ACTIVE INGREDIENTS: OCTINOXATE 60 mg/1 mL; ZINC OXIDE 29.4 mg/1 mL
INACTIVE INGREDIENTS: WATER; TITANIUM DIOXIDE; SILICON DIOXIDE; SILICA DIMETHYL SILYLATE; CYCLOMETHICONE 6; ISODODECANE; LECITHIN, SOYBEAN; HEXAMETHYLENE DIISOCYANATE/TRIMETHYLOL HEXYLLACTONE CROSSPOLYMER; ALCOHOL; DISTEARDIMONIUM HECTORITE; PHENOXYETHANOL; HYDROXYETHYL UREA; CHLORPHENESIN; NYLON-12; FERRIC OXIDE YELLOW; TRIETHOXYCAPRYLYLSILANE; FERRIC OXIDE RED; GLYCERIN; NIACINAMIDE; MALTODEXTRIN; FERROSOFERRIC OXIDE; CETYL PEG/PPG-10/1 DIMETHICONE (HLB 2); PEG-10 DIMETHICONE (220 CST); POLYMETHYLSILSESQUIOXANE/TRIMETHYLSILOXYSILICATE; TRIMETHYLSILOXYSILICATE (M/Q 0.8-1.0); DIMETHICONE/VINYL DIMETHICONE CROSSPOLYMER (SOFT PARTICLE); METHYLPROPANEDIOL; SODIUM PYRROLIDONE CARBOXYLATE; CAPRYLYL GLYCOL; ALPHA-TOCOPHEROL ACETATE; HYALURONATE SODIUM; SILANEDIOL SALICYLATE; TROMETHAMINE; CERAMIDE NP; SODIUM BENZOATE; PROLINE; CALCIUM CITRATE; LAURETH-12; HEXYL LAURATE; POLYMETHYLSILSESQUIOXANE (4.5 MICRONS); ALBIZIA JULIBRISSIN BARK; MAITAKE; POTASSIUM SORBATE; SODIUM ALGINATE; ETHYLHEXYLGLYCERIN; HYDROLYZED SOY PROTEIN (ENZYMATIC; 2000 MW); AMINO ACIDS, RICE; ADANSONIA DIGITATA SEED; PANTHENOL; CYCLOMETHICONE 5; POLYGLYCERYL-4 ISOSTEARATE; VITAMIN A PALMITATE; HYALURONIC ACID; PROPANEDIOL; ACACIA

LBEL CONCENTRE BASE SERUM ANTIEDAD EFECTO LIFTING FPS 15 ANTI AGING LIFTING SERUM FOUNDATION SPF 15

Active Ingredients

OCTINOXATE 6.00%

ZINC OXIDE 2.94%

Purpose

Sunscreen

Uses

- Helps prevent sunburn.

Warnings

- Skin Cancer/Skin Aging Alert: Spending time in the sun increases your risk of skin cancer and early skin aging. This product has been shown only to help prevent sunburn, not skin cancer or early skin aging.
- For external use only.

Do not use

on damaged or broken skin.

When using this product

keep out of eyes. Rinse with water to remove.

Stop use and ask a doctor if

rash occurs.

Keep out of reach of children.

If swallowed, get medical help or contact a Poison Control Center right away.

Directions

- Apply liberally and evenly 15 minutes before sun exposure.
- Reapply at least every 2 hours.
- Use a water resistant sunscreen if swimming or sweating.
- Children under 6 months of age: Ask a doctor

Other information

Protect the product in this container from excessive heat and direct sun.

Inactive ingredients

WATER, CYCLOHEXASILOXANE, ISODODECANE, GLYCERIN, HDI/TRIMETHYLOL HEXYLLACTONE CROSSPOLYMER, ALCOHOL DENAT., NYLON-12, NIACINAMIDE, HYDROXYETHYL UREA, PEG-10 DIMETHICONE, TRIMETHYLSILOXYSILICATE, CETYL PEG/PPG-10/1 DIMETHICONE, POLYMETHYLSILSESQUIOXANE/TRIMETHYLSILOXYSILICATE, SODIUM PCA, POLYMETHYLSILSESQUIOXANE, ALBIZIA JULIBRISSIN BARK EXTRACT, SILICA, POLYSILICONE-11, PHENOXYETHANOL, CYCLOPENTASILOXANE, POLYGLYCERYL-4 ISOSTEARATE, TOCOPHERYL ACETATE, HEXYL LAURATE, SILICA DIMETHYL SILYLATE, METHYLPROPANEDIOL, CAPRYLYL GLYCOL, DISTEARDIMONIUM HECTORITE, CHLORPHENESIN, SILANEDIOL SALICYLATE, FRAGRANCE, RETINYL PALMITATE, ALCOHOL, TROMETHAMINE, ACACIA SENEGAL GUM EXTRACT, PANTHENOL, PROPANEDIOL, CERAMIDE NP, LECITHIN, GRIFOLA FRONDOSA FRUITING BODY EXTRACT, MALTODEXTRIN, HYDROLYZED SOY PROTEIN, POTASSIUM SORBATE, SODIUM BENZOATE, LAURETH-12, RICE AMINO ACIDS, PROLINE, ALGIN, HYALURONIC ACID, SODIUM HYALURONATE, HYDROLYZED ADANSONIA DIGITATA SEED EXTRACT, CALCIUM CITRATE, ETHYLHEXYLGLYCERIN.

MAY CONTAIN :
TITANIUM DIOXIDE, IRON OXIDES, TRIETHOXYCAPRYLYLSILANE.

Company Information

U.S.A & PUERTO RICO: Dist. by Ventura Corp, Ltd., San Juan, Puerto Rico 00926, Made in Colombia.

www.lbel.com